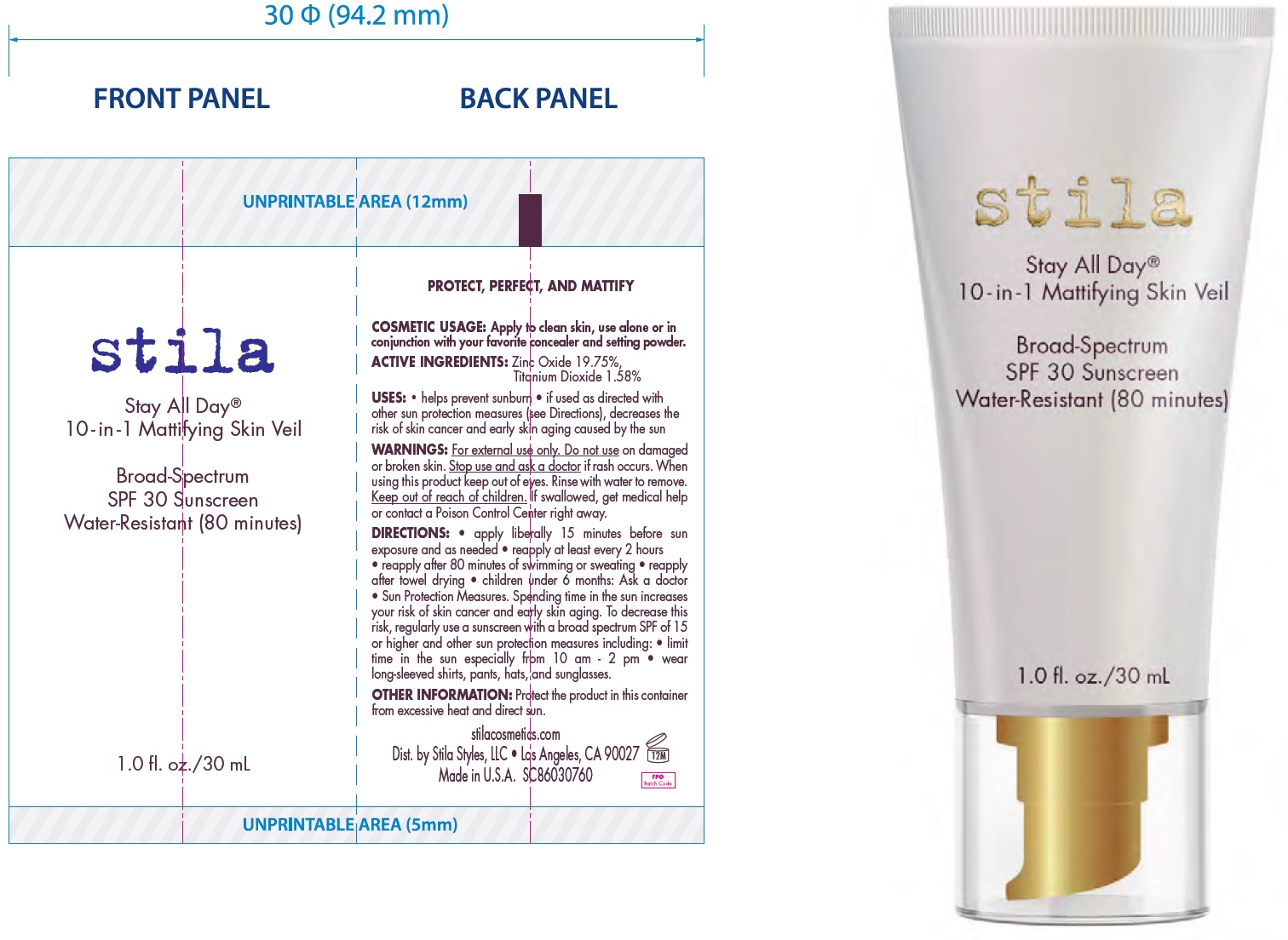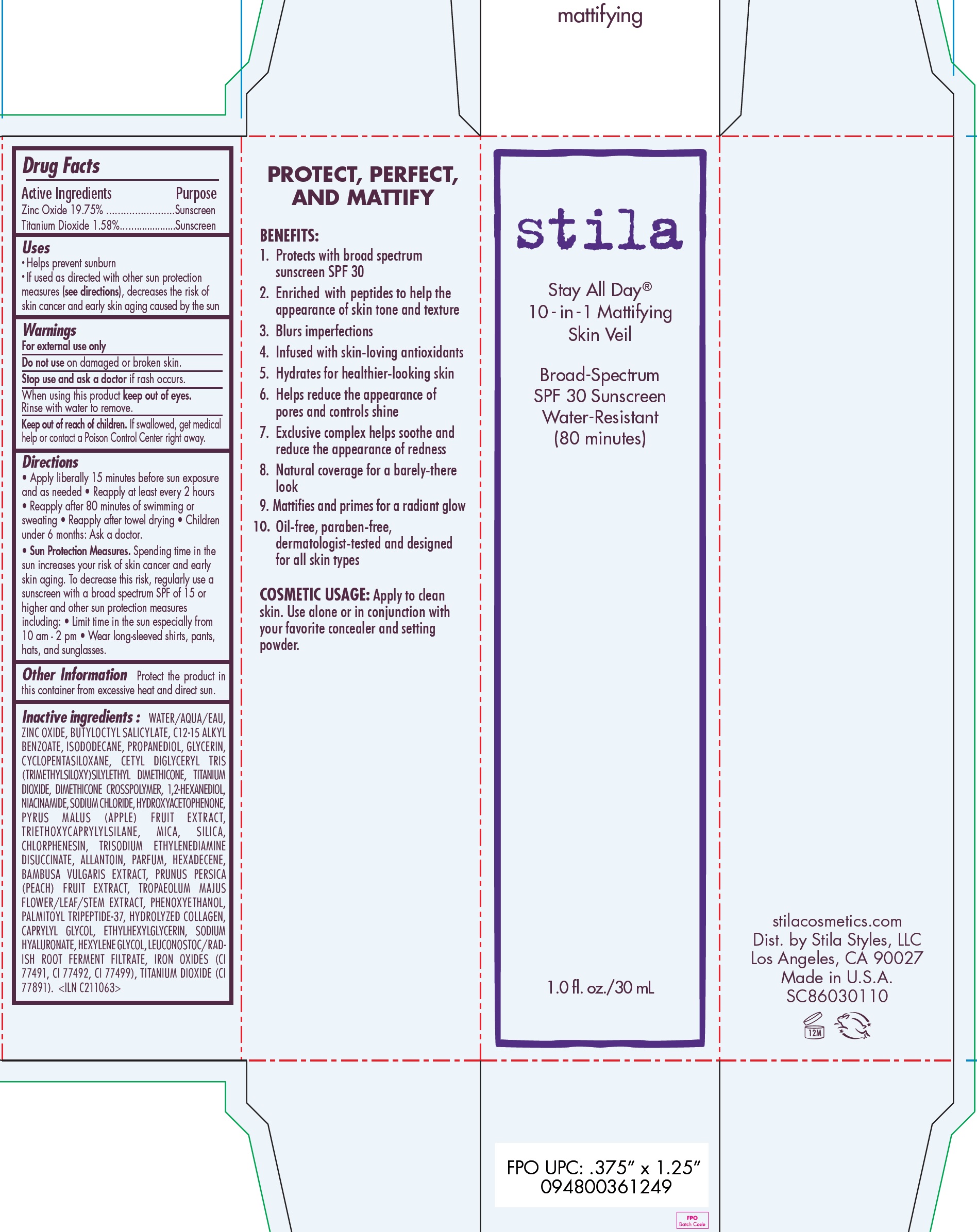 DRUG LABEL: Stay All Day 10-in-1 Mattifying Skin Veil Broad-Spectrum SPF 30 Sunscreen Water-Resistant 80 minutes Mattifying
NDC: 76049-203 | Form: CREAM
Manufacturer: Stila Style, LLC
Category: otc | Type: HUMAN OTC DRUG LABEL
Date: 20220411

ACTIVE INGREDIENTS: ZINC OXIDE 197.5 mg/1 mL; TITANIUM DIOXIDE 15.8 mg/1 mL
INACTIVE INGREDIENTS: WATER; BUTYLOCTYL SALICYLATE; BENZOIC ACID; ISODODECANE; PROPANEDIOL; GLYCERIN; CYCLOMETHICONE 5; 1,2-HEXANEDIOL; NIACINAMIDE; SODIUM CHLORIDE; HYDROXYACETOPHENONE; APPLE; TRIETHOXYCAPRYLYLSILANE; MICA; SILICON DIOXIDE; CHLORPHENESIN; TRISODIUM ETHYLENEDIAMINE DISUCCINATE; ALLANTOIN; HEXADECENE (MIXED ISOMERS); BAMBUSA VULGARIS TOP; PEACH; TROPAEOLUM MAJUS FLOWERING TOP; PHENOXYETHANOL; CAPRYLYL GLYCOL; ETHYLHEXYLGLYCERIN; HYALURONATE SODIUM; HEXYLENE GLYCOL; LEUCONOSTOC/RADISH ROOT FERMENT FILTRATE; FERRIC OXIDE RED; FERRIC OXIDE YELLOW; FERROSOFERRIC OXIDE

Stay All Day® 10-in-1 Mattifying Skin Veil Broad-Spectrum SPF 30 Sunscreen Water-Resistant (80 minutes) - Mattifying

Active Ingredients

Zinc Oxide 19.75%

Titanium Dioxide 1.58%

Purpose

Sunscreen

Uses

• Helps prevent sunburn
• If used as directed with other sun protection measures (see directions), decreases the risk of skin cancer and early skin aging caused by the sun

Warnings

For external use only

Do not use

on damaged or broken skin.

Stop use and ask a doctor

if rash occurs.

When using this product

keep out of eyes. Rinse with water to remove.

Keep out of reach of children.

If swallowed, get medical help or contact a Poison Control Center right away.

Directions

• Apply liberally 15 minutes before sun exposure and as needed • Reapply at least every 2 hours • Reapply after 80 minutes of swimming or sweating • Reapply after towel drying • Children under 6 months: Ask a doctor. • Sun Protection Measures. Spending time in the sun increases your risk of skin cancer and early skin aging. To decrease this risk, regularly use a sunscreen with a broad spectrum SPF of 15 or higher and other sun protection measures including: • Limit time in the sun especially from 10 am - 2 pm • Wear long-sleeved shirts, pants, hats, and sunglasses.

Other Information

Protect the product in this container from excessive heat and direct sun.

Inactive ingredients :

WATER/AQUA/EAU, ZINC OXIDE, BUTYLOCTYL SALICYLATE, C12-15 ALKYL BENZOATE, ISODODECANE, PROPANEDIOL, GLYCERIN,
CYCLOPENTASILOXANE, CETYL DIGLYCERYL TRIS (TRIMETHYLSILOXY)SILYLETHYL DIMETHICONE, TITANIUM DIOXIDE, DIMETHICONE CROSSPOLYMER, 1,2-HEXANEDIOL, NIACINAMIDE, SODIUM CHLORIDE, HYDROXYACETOPHENONE, PYRUS MALUS (APPLE) FRUIT EXTRACT, TRIETHOXYCAPRYLYLSILANE, MICA, SILICA, CHLORPHENESIN, TRISODIUM ETHYLENEDIAMINE DISUCCINATE, ALLANTOIN, PARFUM, HEXADECENE, BAMBUSA VULGARIS EXTRACT, PRUNUS PERSICA (PEACH) FRUIT EXTRACT, TROPAEOLUM MAJUS FLOWER/LEAF/STEM EXTRACT, PHENOXYETHANOL, PALMITOYL TRIPEPTIDE-37, HYDROLYZED COLLAGEN, CAPRYLYL GLYCOL, ETHYLHEXYLGLYCERIN, SODIUM HYALURONATE, HEXYLENE GLYCOL, LEUCONOSTOC/RADISH ROOT FERMENT FILTRATE, IRON OXIDES (CI 77491, CI 77492, CI 77499), TITANIUM DIOXIDE (CI
77891). <ILN C211063>